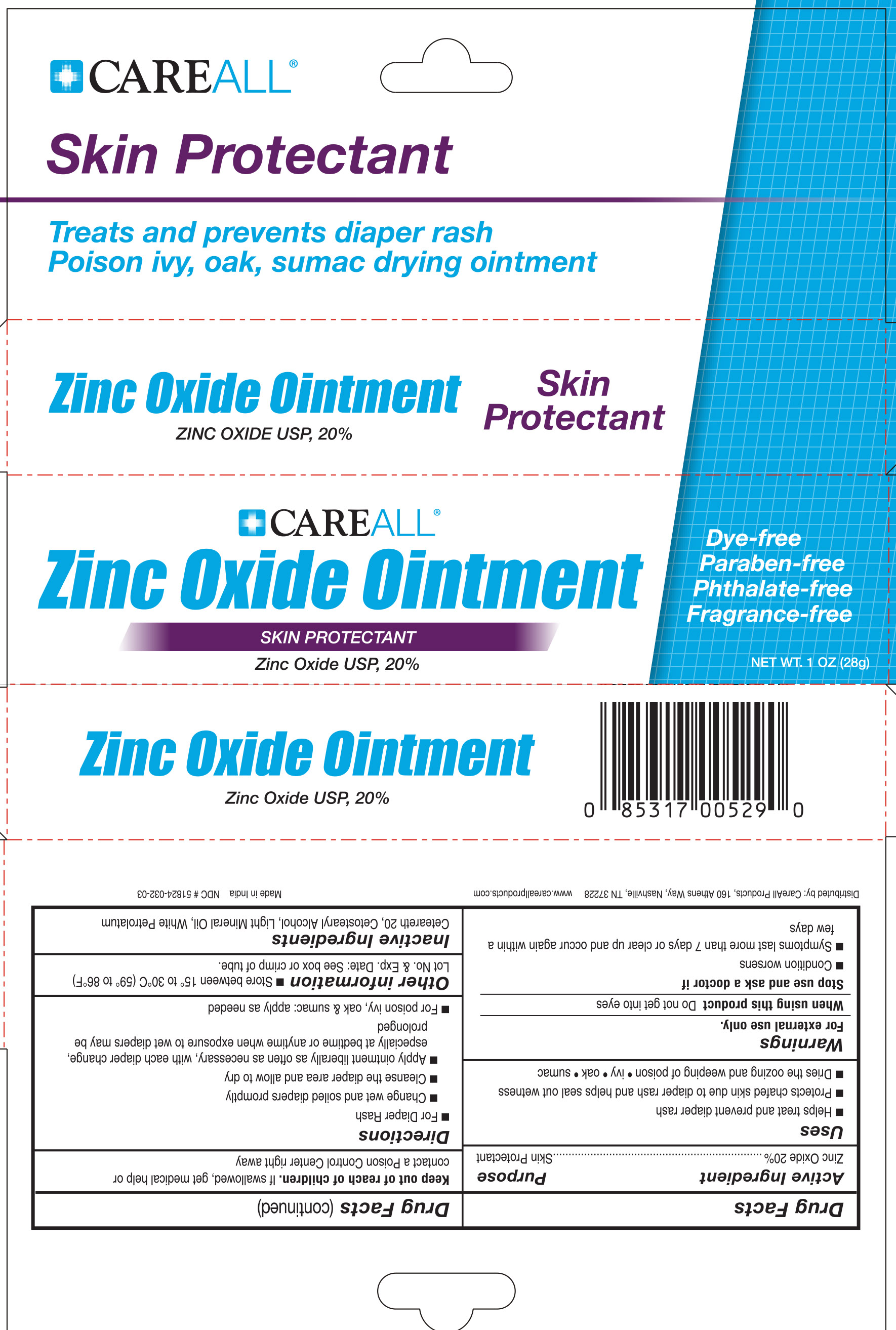 DRUG LABEL: CAREALL Zinc Oxide
NDC: 51824-032 | Form: OINTMENT
Manufacturer: New World Imports Inc
Category: otc | Type: HUMAN OTC DRUG LABEL
Date: 20251201

ACTIVE INGREDIENTS: ZINC OXIDE 0.2 g/1 g
INACTIVE INGREDIENTS: CETOSTEARYL ALCOHOL; POLYOXYL 20 CETOSTEARYL ETHER; LIGHT MINERAL OIL; WHITE PETROLATUM

Drug Facts

ACTIVE INGREDIENT

Zinc Oxide 20%

PURPOSE

Skin Protectant

Keep out of reach of children.If swallowed, get medical help or contact a Poison Control Center right away.

INDICATIONS AND USAGE

- Helps treat and prevent diaper rash
- protects chafed skin due to diaper rash and helps seal out wetness
- Dries the oozing and weeping of poison ivy, poison oak, and poison sumac

WARNINGS

For external use only.

When using this product Do not get into eyes

Stop use and ask a doctor if

- condition worsens
- symptoms last more than 7 days or clear up and occur again within a few days

DOSAGE AND ADMINISTRATION

For Diaper Rash:

- Change wet and soild diapers promptly
- Cleanse the diaper area and allow to dry
- Apply ointment liberally as often as necessary, with each diaper change, especially at bedtime or anytime when exposure to wet diapers may be prolonged

For Poison Ivy, oak and sumac:

- Apply as needed

INACTIVE INGREDIENT

Ceteareth 20, Cetostearyl Alcohol, Light Mineral Oil, White Petrolatum